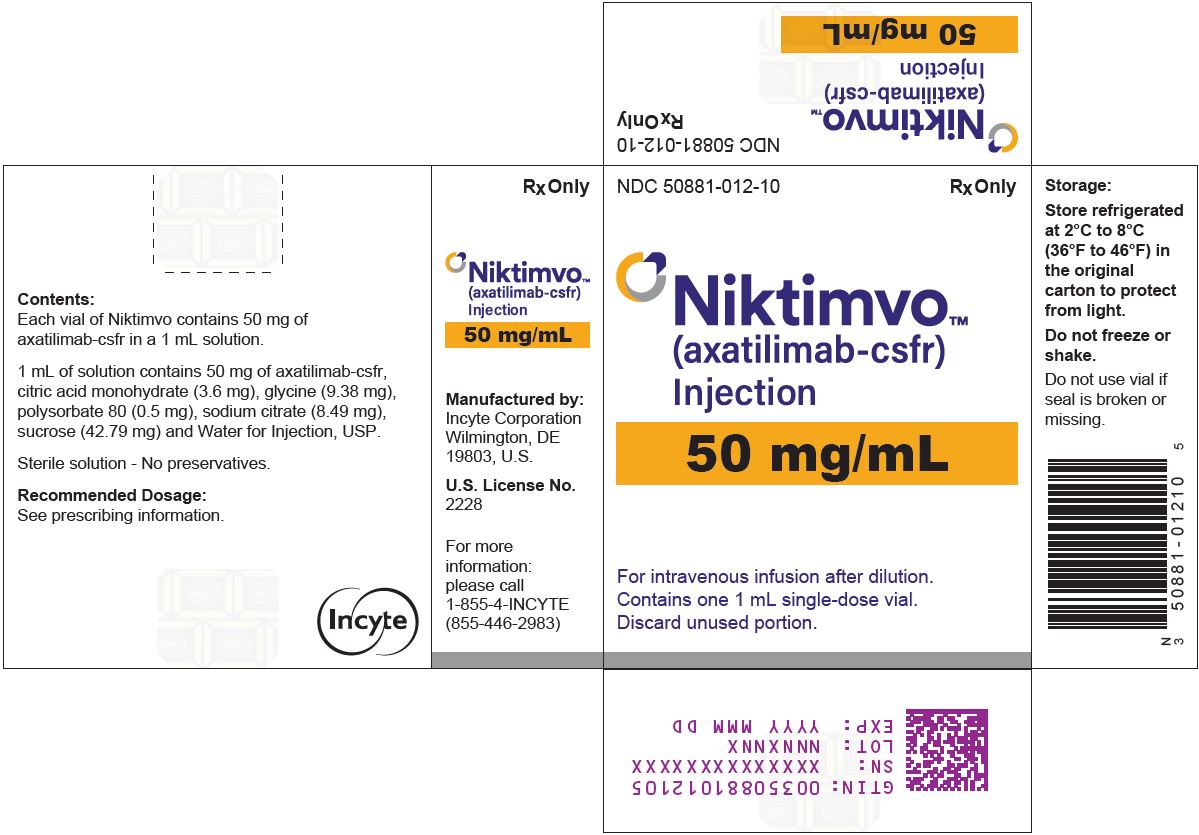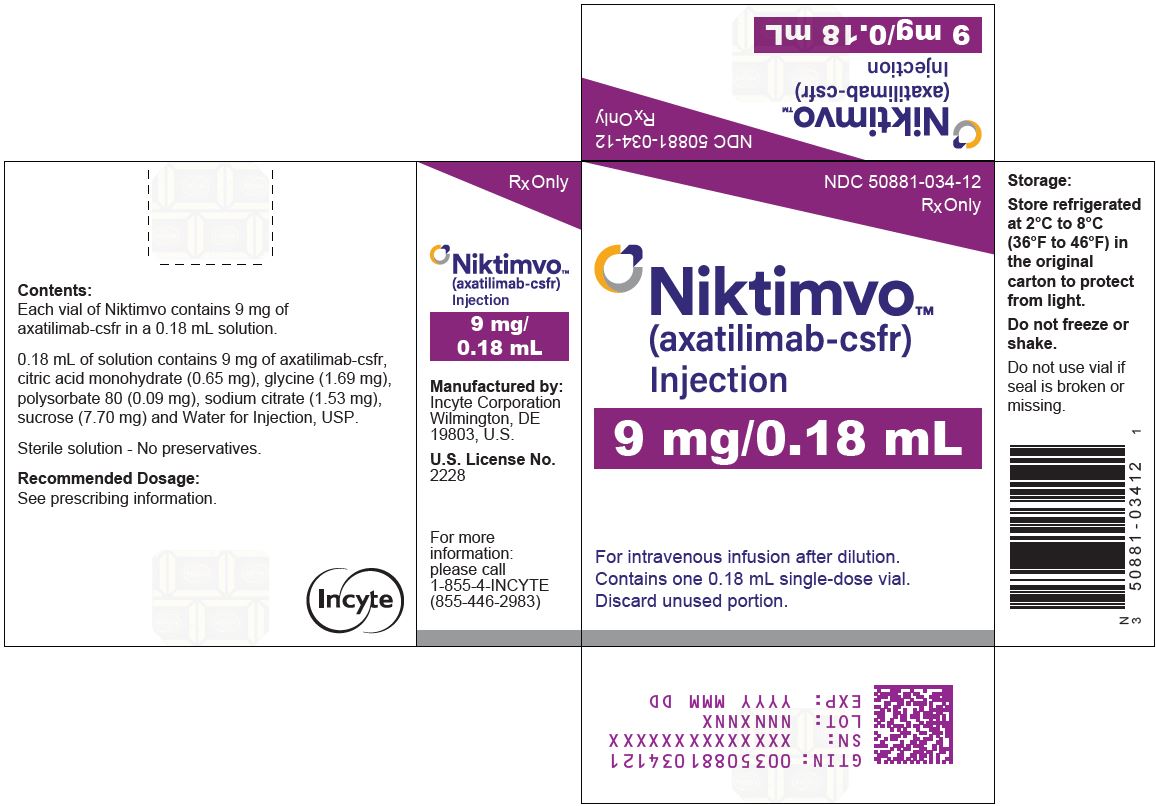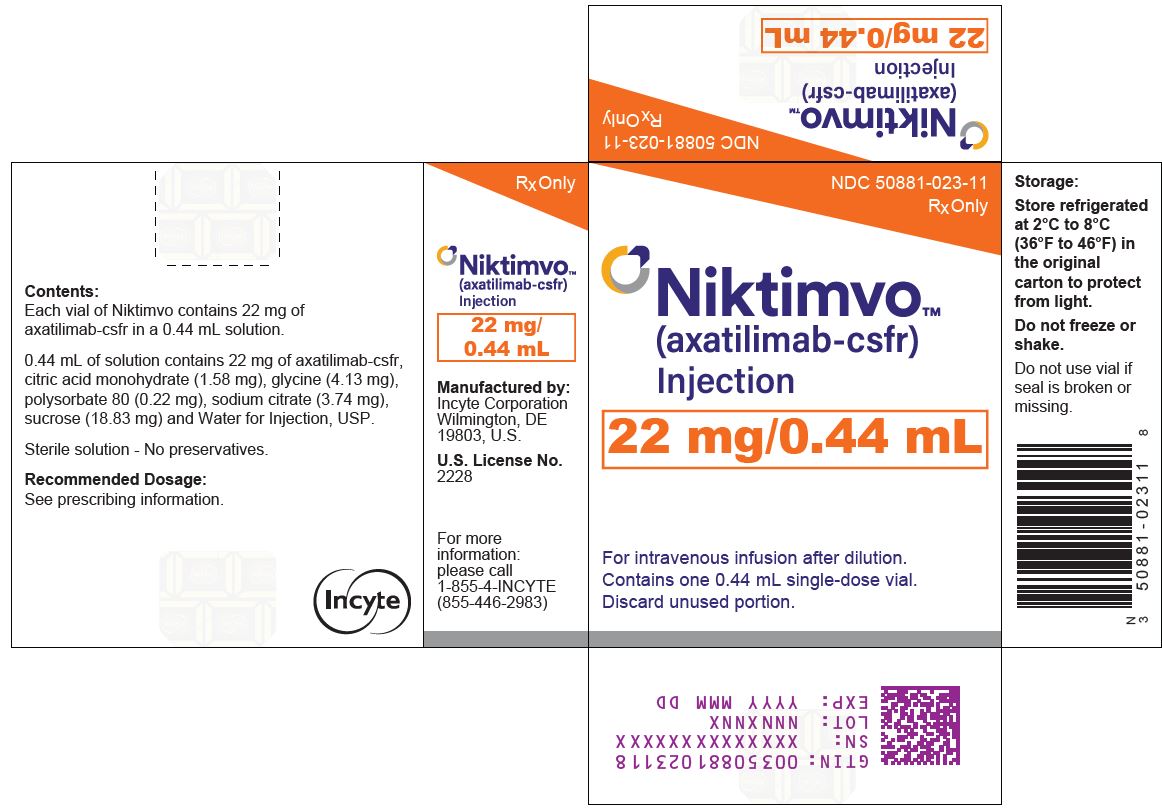 DRUG LABEL: NIKTIMVO
NDC: 50881-012 | Form: INJECTION
Manufacturer: Incyte Corporation
Category: prescription | Type: HUMAN PRESCRIPTION DRUG LABEL
Date: 20250116

ACTIVE INGREDIENTS: AXATILIMAB 50 mg/1 mL
INACTIVE INGREDIENTS: CITRIC ACID MONOHYDRATE 3.60 mg/1 mL; GLYCINE 9.38 mg/1 mL; POLYSORBATE 80 0.50 mg/1 mL; SODIUM CITRATE 8.49 mg/1 mL; SUCROSE 42.79 mg/1 mL; WATER

HIGHLIGHTS OF PRESCRIBING INFORMATION

These highlights do not include all the information needed to use NIKTIMVO safely and effectively. See full prescribing information for NIKTIMVO.
NIKTIMVO™ (axatilimab-csfr) injection, for intravenous use
Initial U.S. Approval: 2024

RECENT MAJOR CHANGES

Dosage and Administration (2.3) | 1/2025

1 INDICATIONS AND USAGE

NIKTIMVO is a colony stimulating factor-1 receptor (CSF-1R)-blocking antibody indicated for the treatment of chronic graft-versus-host disease (cGVHD) after failure of at least two prior lines of systemic therapy in adult and pediatric patients weighing at least 40 kg. (1)

2 DOSAGE AND ADMINISTRATION

- Administer only as an intravenous infusion over 30 minutes. (2.3)
- The recommended dosage of NIKTIMVO is 0.3 mg/kg (maximum 35 mg) every 2 weeks in adult and pediatric patients weighing 40 kg and above. (2.1)

See Full Prescribing Information for dosage modifications for adverse reactions (2.2) and preparation and administration instructions. (2.3)

3 DOSAGE FORMS AND STRENGTHS

Injection: 9 mg/0.18 mL solution in a single-dose vial. (3)

Injection: 22 mg/0.44 mL solution in a single-dose vial. (3)

Injection: 50 mg/mL solution in a single-dose vial. (3)

4 CONTRAINDICATIONS

None. (4)

5 WARNINGS AND PRECAUTIONS

- Infusion-Related Reactions: Interrupt or slow the rate of infusion or permanently discontinue NIKTIMVO based on severity of reaction. (2.2, 5.1)
- Embryo-Fetal Toxicity: May cause fetal harm. Advise females of reproductive potential of the potential risk to a fetus and to use effective contraception. (5.2, 8.1, 8.3)

6 ADVERSE REACTIONS

The most common (≥ 15%) adverse reactions, including laboratory abnormalities, are increased AST, infection (pathogen unspecified), increased ALT, decreased phosphate, decreased hemoglobin, viral infection, increased GGT, musculoskeletal pain, increased lipase, fatigue, increased amylase, increased calcium, increased CPK, increased ALP, nausea, headache, diarrhea, cough, bacterial infection, pyrexia, and dyspnea. (6.1)

To report SUSPECTED ADVERSE REACTIONS, contact Incyte Corporation at 1-855-463-3463 or FDA at 1-800-FDA-1088 or www.fda.gov/medwatch.

8 USE IN SPECIFIC POPULATIONS

Lactation: Advise not to breastfeed. (8.2)

FULL PRESCRIBING INFORMATION

1 INDICATIONS AND USAGE

NIKTIMVO is indicated for the treatment of chronic graft-versus-host disease (cGVHD) after failure of at least two prior lines of systemic therapy in adult and pediatric patients weighing at least 40 kg.

2 DOSAGE AND ADMINISTRATION

2.1 Recommended Dosage

For patients weighing at least 40 kg, administer NIKTIMVO 0.3 mg/kg, up to a maximum dose of 35 mg, as an intravenous infusion over 30 minutes every 2 weeks until progression or unacceptable toxicity.

2.2 Dosage Modifications for Adverse Reactions

Monitor aspartate aminotransferase (AST), alanine aminotransferase (ALT), alkaline phosphatase (ALP), creatine phosphokinase (CPK), amylase, and lipase prior to the start of NIKTIMVO therapy, every 2 weeks for the first month, and every 1 to 2 months thereafter until abnormalities are resolved.
For recommended NIKTIMVO dosage modifications due to adverse reactions, see Table 1.

Table 1: Recommended NIKTIMVO Dosage Modifications for Adverse Reactions
Adverse Reaction | Severity [Graded per National Cancer Institute (NCI) Common Terminology Criteria for Adverse Events (CTCAE) v5.] | Dosage Modification
Infusion-related reactions [see Warnings and Precautions (5.1)] | Grade 1 or 2 | - Temporarily interrupt the infusion until resolution or decrease infusion rate by 50%. - Initiate symptomatic treatment (e.g., antihistamines and antipyretics). - For subsequent infusions, premedicate and resume the infusion at 50% of the prior infusion rate.
Infusion-related reactions [see Warnings and Precautions (5.1)] | Grade 3 or 4 | Permanently discontinue NIKTIMVO.
Elevation of AST or ALT (on the day of dosing) [see Adverse Reactions (6.1)] | Grade 3 with total bilirubin ≤ Grade 1 | Withhold NIKTIMVO until recovery to Grade 2, then resume NIKTIMVO at 0.2 mg/kg (maximum 23 mg) every 2 weeks.
Elevation of AST or ALT (regardless of the time of the reaction) [see Adverse Reactions (6.1)] | ALT or AST ≥ 3 times ULN with total bilirubin ≥ 2 times ULN and ALP < 2 times ULN | Withhold NIKTIMVO and investigate for drug-induced liver injury. If confirmed, permanently discontinue NIKTIMVO.
Elevation of AST or ALT (regardless of the time of the reaction) [see Adverse Reactions (6.1)] | Grade 4 | Permanently discontinue NIKTIMVO.
Elevation of CPK, amylase, or lipase [see Adverse Reactions (6.1)] | ≥ Grade 3 | - If diagnostic evaluation results show no evidence of end-organ damage, continue NIKTIMVO without dose reduction. - If diagnostic evaluation results show evidence of end-organ damage, permanently discontinue NIKTIMVO.
Elevation of CPK, amylase, or lipase [see Adverse Reactions (6.1)] | Symptomatic ≥ Grade 3 | Permanently discontinue NIKTIMVO.
Other Nonhematologic Adverse Reactions [see Adverse Reactions (6.1)] | Grade 3 | Withhold NIKTIMVO until recovery to Grade 2:; - If delayed by ≤ 4 weeks from the planned infusion, resume NIKTIMVO at 0.2 mg/kg (maximum 23 mg) every 2 weeks. - If delayed by > 4 weeks from the planned infusion, permanently discontinue NIKTIMVO.
Other Nonhematologic Adverse Reactions [see Adverse Reactions (6.1)] | Grade 4 | Permanently discontinue NIKTIMVO.
AST = aspartate aminotransferase; ALT = alanine aminotransferase; ULN = upper limit of normal; ALP = alkaline phosphatase; CPK = creatine phosphokinase.

2.3 Preparation and Administration

Preparation

- Use aseptic technique to prepare NIKTIMVO.
- Visually inspect the vial for particulate matter and discoloration prior to dilution. NIKTIMVO is a slightly opalescent, pale brownish yellow solution. Discard the vial if the solution is cloudy, discolored, or contains visible particles.
- Do not shake the vial.
- Determine the dose [see Dosage and Administration (2.1)] and total volume of NIKTIMVO solution needed. Each mL of NIKTIMVO contains 50 mg of axatilimab-csfr.

Dilution

- Withdraw the calculated volume of NIKTIMVO solution from the vial and add it into an intravenous infusion bag made of polyvinyl chloride (PVC), polyolefin, polyolefin with polyamide, or ethylene vinyl acetate (EVA) containing 0.9% Sodium Chloride Injection to achieve a final concentration between the range of 0.24 mg/mL and 0.75 mg/mL.
- Discard vial with any unused portion.
- Mix diluted solution by gentle inversion. Do not shake.
- Parenteral drug products should be inspected visually for particulate matter and discoloration prior to administration, whenever solution and container permit. The diluted solution is a clear to slightly opalescent, colorless solution that may contain trace amounts of translucent to white particles. Discard if the solution is cloudy, discolored, or contains extraneous particulate matter other than trace amounts of translucent to white particles.

Storage of diluted NIKTIMVO solution

- Immediately use diluted NIKTIMVO solution. If not used immediately, the diluted solution can be stored:
  - At room temperature [up to 25°C (77°F)] for no more than 4 hours from the time of preparation to the end of the infusion.
  OR
  - Refrigerated at 2°C to 8°C (36°F to 46°F) for no more than 24 hours. If refrigerated, allow the diluted solution to come to room temperature prior to administration. The diluted solution must be administered within 4 hours (including infusion time) once it is removed from the refrigerator.

- Do not freeze or shake the diluted solution.

Administration

- Administer diluted NIKTIMVO solution by intravenous infusion over 30 minutes through a dedicated infusion line that includes a sterile, low-protein binding 0.2-micron in-line or add-on polyethersulfone (PES) filter.
- Do not co‑administer other drugs through the same infusion line.
- After administration, flush the infusion line with 0.9% Sodium Chloride Injection.

3 DOSAGE FORMS AND STRENGTHS

NIKTIMVO injection is a slightly opalescent, pale brownish yellow solution available as:

- 9 mg/0.18 mL in a single-dose vial.
- 22 mg/0.44 mL in a single-dose vial.
- 50 mg/mL in a single-dose vial.

4 CONTRAINDICATIONS

None.

5 WARNINGS AND PRECAUTIONS

5.1 Infusion-Related Reactions

NIKTIMVO can cause infusion-related reactions. Infusion-related reactions, including hypersensitivity reactions, occurred in 18% of patients who received NIKTIMVO in the clinical trial (AGAVE-201), with Grade 3 or 4 reactions in 1.3% [see Adverse Reactions (6.1)].
Premedicate with an antihistamine and an antipyretic for patients who have previously experienced an infusion-related reaction to NIKTIMVO [see Dosage and Administration (2.2)]. Monitor patients for signs and symptoms of infusion-related reactions, including fever, chills, rash, flushing, dyspnea, and hypertension. Interrupt or slow the rate of infusion or permanently discontinue NIKTIMVO based on severity of the reaction [see Dosage and Administration (2.2)].

5.2 Embryo-Fetal Toxicity

Based on its mechanism of action, NIKTIMVO may cause fetal harm when administered to a pregnant woman. Advise pregnant women of the potential risk to the fetus. Advise females of reproductive potential to use effective contraception during treatment with NIKTIMVO and for 30 days after the last dose [see Use in Specific Populations (8.1, 8.3)].

6 ADVERSE REACTIONS

The following adverse reactions are described elsewhere in the labeling.

- Infusion-Related Reactions [see Warnings and Precautions (5.1)]

6.1 Clinical Trial Experience

Because clinical trials are conducted under widely varying conditions, adverse reaction rates observed in the clinical trials of a drug cannot be directly compared to rates in the clinical trials of another drug and may not reflect the rates observed in practice.

Chronic Graft-Versus-Host Disease

The safety of NIKTIMVO was evaluated in 79 adult and pediatric patients with cGVHD treated with NIKTIMVO 0.3 mg/kg intravenously every 2 weeks in the AGAVE‑201 trial [see Clinical Studies (14)]. The median duration of treatment was 10.3 months (range: 0.5 to 28.6 months), and 73.4% were treated for more than 6 months.

Serious adverse reactions occurred in 44% of patients who received NIKTIMVO. Serious adverse reactions in more than 2 patients included infection (pathogen unspecified), viral infection, and respiratory failure. Permanent discontinuation of NIKTIMVO due to an adverse reaction occurred in 10% of patients and dose reduction due to adverse reaction occurred in 8% of patients. Dose interruptions due to an adverse reaction occurred in 44% of patients. The adverse reactions leading to dose interruption in more than 2 patients were viral infection, infection (pathogen unspecified), bacterial infection, musculoskeletal pain, and pyrexia.

The most common (≥ 15%) adverse reactions, including laboratory abnormalities, were increased AST, infection (pathogen unspecified), increased ALT, decreased phosphate, decreased hemoglobin, viral infection, increased gamma glutamyl transferase (GGT), musculoskeletal pain, increased lipase, fatigue, increased amylase, increased calcium, increased CPK, increased ALP, nausea, headache, diarrhea, cough, bacterial infection, pyrexia, and dyspnea.

Table 2 summarizes the nonlaboratory adverse reactions in AGAVE-201.

Table 2: Adverse Reactions in ≥ 10% of Patients With cGVHD Who Received NIKTIMVO in AGAVE-201
Adverse Reaction | NIKTIMVO 0.3 mg/kg intravenously every 2 weeks (N = 79)
Adverse Reaction | All Grades (%) | Grades 3-4 (%)
Infections and infestations
Infection (pathogen unspecified) [Includes abscess jaw, atypical pneumonia, bacteremia, bronchitis, conjunctivitis, cystitis, device-related infection, enterocolitis infectious, gastroenteritis, gastrointestinal infection, groin abscess, hordeolum, liver abscess, nasopharyngitis, otitis media, otitis media acute, pneumonia, respiratory tract infection, rhinitis, sepsis, sinusitis, tooth infection, upper respiratory tract infection, urinary tract infection, and wound infection.] | 57 | 14
Viral infection [Includes adenoviral upper respiratory infection, BK virus infection, COVID-19, coronavirus infection, enterovirus infection, gastroenteritis astroviral, gastroenteritis viral, herpes simplex, herpes zoster, influenza, metapneumovirus bronchiolitis, metapneumovirus infection, norovirus infection, oral viral infection, parainfluenza viral bronchitis, parainfluenza virus infection, respiratory syncytial virus infection, rhinovirus infection, viral infection, and viral upper respiratory tract infection.] | 43 | 15
Bacterial infection [Includes bacterial diarrhea, bacterial vaginosis, campylobacter gastroenteritis, campylobacter infection, cellulitis, clostridium difficile colitis, clostridium difficile infection, enterococcal infection, erysipelas, hemophilus infection, lower respiratory tract infection bacterial, pseudomonal skin infection, staphylococcal bacteremia, staphylococcal infection, stenotrophomonas infection, streptococcal infection, and urinary tract infection enterococcal.] | 15 | 8
Musculoskeletal and connective tissue disorders
Musculoskeletal pain [Includes arthralgia, back pain, flank pain, musculoskeletal pain, myalgia, pain in extremity.] | 35 | 3
General disorders and administration site conditions
Fatigue [Includes asthenia, fatigue, and malaise.] | 32 | 4
Pyrexia | 15 | 1
Edema [Includes localized edema and peripheral edema.] | 13 | 1
Gastrointestinal disorders
Nausea [Includes nausea and vomiting.] | 23 | 3
Diarrhea [Includes colitis and diarrhea.] | 18 | 5
Nervous system disorders
Headache [Includes headache and migraine.] | 20 | 1
Dizziness [Includes dizziness and dizziness postural.] | 11 | 0
Respiratory, thoracic and mediastinal disorders
Cough [Includes cough and productive cough.] | 18 | 0
Dyspnea [Includes dyspnea and dyspnea exertional.] | 15 | 3
Immune system disorders
Drug hypersensitivity [Includes bronchospasm, flushing, hot flush, hypersensitivity, infusion-related hypersensitivity reaction, infusion-related reaction, and urticaria.] | 13 | 3
Metabolism and nutrition disorders
Decreased appetite | 11 | 4
Vascular disorders
Hemorrhage [Includes contusion, epistaxis, hematochezia, hematoma, and vaginal hemorrhage.] | 11 | 1
Skin and subcutaneous tissue disorders
Rash [Includes dermatitis bullous, dermatitis exfoliative generalized, rash, and rash maculo-papular.] | 10 | 0
Graded according to NCI CTCAE v5.0.

Clinically relevant adverse reactions in < 10% of patients who received NIKTIMVO included:

- Eye disorders: periorbital edema
- Skin and subcutaneous skin disorders: pruritus
- Vascular disorders: hypertension

Table 3 summarizes the laboratory abnormalities in AGAVE-201.

Table 3: Selected Laboratory Abnormalities in Patients with cGVHD Who Received NIKTIMVO in AGAVE-201
Laboratory Abnormality | NIKTIMVO 0.3 mg/kg intravenously every 2 weeks (N=79)
Laboratory Abnormality | All Grades [The denominator used to calculate the rate varied from 78 to 79 based on the number of patients with at least 1 post-treatment value.] (%) | Grade 3 or 4 (%)
Hematology
Decreased hemoglobin | 48 | 4
Chemistry
Increased aspartate aminotransferase | 61 | 5
Increased alanine aminotransferase | 51 | 3
Decreased phosphate | 51 | NA
Increased gamma glutamyl transferase | 39 | 4
Increased lipase | 34 | 3
Increased amylase | 32 | 0
Increased calcium | 31 | 1
Increased alkaline phosphatase | 28 | 0
Increased creatine phosphokinase | 25 | 0
NA = not applicable.

Immunogenicity: Anti-Drug Antibody–Associated Adverse Reactions

In 276 patients with cGVHD who received NIKTIMVO in clinical trials, among the patients who developed anti-drug antibodies (ADAs), hypersensitivity reactions occurred in 26% (13/50) of patients with neutralizing antibodies (NAb) and in 4% (2/45) of those without NAb [see Clinical Pharmacology (12.6)].

8 USE IN SPECIFIC POPULATIONS

8.1 Pregnancy

Risk Summary

Based on its mechanism of action, NIKTIMVO may cause fetal harm when administered to pregnant women [see Clinical Pharmacology (12.1)]. There are no available data on the use of NIKTIMVO in pregnant women to evaluate for a drug-associated risk. No animal reproductive and developmental toxicity studies have been conducted with axatilimab-csfr.

Targeted mutation of CSF-1R or CSF-1 in rodent models results in prenatal and perinatal death, deficits in growth, and pleiotropic impact on multiple organ systems, including skeletal and reproductive. Regulation by CSF-1R on non-mononuclear phagocytic cells and macrophages plays a role in the innate immune protection of the fetus and in pregnancy maintenance and embryo-fetal development. Human immunoglobulin G (IgG) is known to cross the placenta; therefore, NIKTIMVO has the potential to be transmitted from the mother to the developing fetus. Advise women of the potential risk to the fetus.

In the U.S. general population, the estimated background risk of major birth defects and miscarriage in clinically recognized pregnancies is 2% to 4% and 15% to 20%, respectively.

8.2 Lactation

Risk Summary
There are no data on the presence of axatilimab-csfr in human milk or the effects on the breastfed child or milk production. Maternal IgG is known to be present in human milk. Because of the potential for serious adverse reactions in a breastfed child, advise women not to breastfeed during treatment and for 30 days after the last dose of NIKTIMVO.

8.3 Females and Males of Reproductive Potential

NIKTIMVO may cause fetal harm when administered to a pregnant woman [see Use in Specific Populations (8.1)].
Pregnancy Testing
Verify pregnancy status in females of reproductive potential prior to initiating NIKTIMVO [see Use in Specific Populations (8.1)].
Contraception
Females
Advise females of reproductive potential to use effective contraception during treatment with NIKTIMVO and for 30 days after the last dose of NIKTIMVO.

8.4 Pediatric Use

The safety and effectiveness of NIKTIMVO for the treatment of cGVHD after failure of at least two prior lines of systemic therapy have been established in pediatric patients weighing at least 40 kg. Use of NIKTIMVO in pediatric patients weighing at least 40 kg is supported by evidence from clinical trials that included 3 children (ages 6 to less than 12 years old) and 5 adolescents (ages 12 to less than 17 years old) [see Clinical Studies (14)]. The safety and effectiveness of NIKTIMVO have not been established in pediatric patients weighing less than 40 kg.
Compared to adult and pediatric patients weighing 40 kg and above, patients weighing less than 40 kg had lower maximum concentration, trough concentration, and average concentration at the same weight-based dosage.
Based on findings of thickening of the growth plate and metaphysis and/or degeneration of the growth plate in the femur in animals, monitor bone growth and development in pediatric patients [see Nonclinical Toxicology (13.2)].

8.5 Geriatric Use

Of the 79 patients with cGVHD treated with NIKTIMVO, 21 (26.6%) were 65 years and older, and 2 (2.5%) were 75 years and older [see Clinical Studies (14)]. No overall differences in the safety or effectiveness of NIKTIMVO have been observed between patients 65 years of age and older and younger patients.

11 DESCRIPTION

Axatilimab-csfr is a CSF-1R–blocking antibody. Axatilimab-csfr is a humanized IgG4 (kappa light chain) monoclonal antibody produced in Chinese hamster ovary cells. Axatilimab-csfr has an approximate molecular weight of 150 kDa.
NIKTIMVO (axatilimab-csfr) injection is a sterile, preservative-free, slightly opalescent, pale brownish yellow solution for intravenous use. The solution is free from visible particles.
Each single-dose vial contains 9 mg, 22 mg, or 50 mg of axatilimab-csfr at a concentration of 50 mg/mL. Each mL of solution contains citric acid monohydrate (3.6 mg), glycine (9.38 mg), polysorbate 80 (0.5 mg), sodium citrate (8.49 mg), sucrose (42.79 mg) and Water for Injection, USP. The pH is 5.0.

12 CLINICAL PHARMACOLOGY

12.1 Mechanism of Action

Axatilimab-csfr is a monoclonal antibody that binds to colony stimulating factor-1 receptors (CSF-1R) expressed on monocytes and macrophages. Blocking CSF-1R with axatilimab-csfr reduces the levels of these circulating proinflammatory and profibrotic monocytes and monocyte-derived macrophages, as demonstrated by a reduction of nonclassical monocyte counts in nonclinical studies with axatilimab-csfr, and inhibits the activity of pathogenic macrophages in tissues.

12.2 Pharmacodynamics

CSF-1 and Interleukin (IL)-34
Axatilimab-csfr caused a dose-dependent increase from 0.15 mg/kg to 6 mg/kg (0.5 to 20 times the approved recommended dosage) in CSF-1 and interleukin (IL)-34 concentrations and a dose-dependent reduction in the levels of nonclassical monocytes in peripheral blood.

12.3 Pharmacokinetics

Axatilimab-csfr pharmacokinetics are presented as geometric mean (coefficient of variation [%CV]) in adult patients with cGVHD following axatilimab-csfr 0.3 mg/kg (maximum 35 mg) every 2 weeks, unless otherwise specified. Axatilimab-csfr AUC increased in a greater than dose-proportional manner following single-dose administration of axatilimab-csfr over a dose range of 0.15 mg/kg to 3 mg/kg (0.5 to 10 times the approved recommended dosage) in healthy subjects.

There was no axatilimab-csfr systemic accumulation following the approved recommended dosage.

Distribution

Axatilimab-csfr volume of distribution is 6.06 L (16.3% CV).

Elimination

Axatilimab-csfr total clearance is 0.07 L/h (38.8% CV). The median (5th to 95th percentile) time to 97% reduction from Cmax after the end of infusion is 4.0 (2.3 to 7.2) days following axatilimab-csfr 0.3 mg/kg (maximum 35 mg).

The total clearance of axatilimab-csfr is composed of linear and non-linear components such that axatilimab-csfr clearance decreased from 2.32 mL/h/kg to 0.21 mL/h/kg and mean terminal half-life increased from 10.7 hours to 108 hours following single-dose administrations of axatilimab-csfr over a dose range of 0.15 mg/kg to 3 mg/kg (0.5 to 10 times the approved recommended dosage).

Metabolism

Axatilimab-csfr is expected to be metabolized into small peptides by catabolic pathways.

Specific Populations

No clinically meaningful differences in the exposure of axatilimab-csfr were observed in adult and pediatric patients based on age (12 to 81 years), sex, body weight (40 to 151 kg), race (White, Black, or Asian), mild to moderate renal impairment (estimated creatinine clearance 30-89 mL/min by the Cockcroft-Gault equation), or mild hepatic impairment (total bilirubin ≤ ULN and AST > ULN or total bilirubin 1 to ≤ 1.5 times ULN and any AST) following the approved recommended dosage of 0.3 mg/kg (maximum 35 mg) every 2 weeks.

The effect of severe renal impairment (estimated creatinine clearance 15-29 mL/min, Cockcroft-Gault equation) and moderate to severe hepatic impairment (total bilirubin > 1.5 times ULN and any AST) on axatilimab-csfr pharmacokinetics is unknown.

Pediatric Patients

Axatilimab-csfr exposures in pediatric patients weighing 40 kg and above are comparable to those in adults following the approved recommended dosage of 0.3 mg/kg (maximum 35 mg) every 2 weeks.

12.6 Immunogenicity

The observed incidence of ADAs is highly dependent on the sensitivity and specificity of the assay. Differences in assay methods preclude meaningful comparisons of the incidence of ADAs in the studies described below with the incidence of ADAs in other studies, including those of NIKTIMVO or of other axatilimab products.
ADAs were assessed in 276 patients with cGVHD who received NIKTIMVO. The incidence of axatilimab-csfr treatment-emergent ADAs was 33.7% (93/276) following a median exposure time of 7.8 months. NAb were detected in 47 of 93 cGVHD patients with treatment-emergent ADAs. There was no clinically meaningful effect of anti–axatilimab-csfr antibodies or NAb on the pharmacokinetics, pharmacodynamics, or effectiveness of NIKTIMVO. The presence of NAb correlated with the occurrence of hypersensitivity reactions [see Adverse Reactions (6.1)].

13 NONCLINICAL TOXICOLOGY

13.1 Carcinogenesis, Mutagenesis, Impairment of Fertility

No studies have been performed to assess the potential of axatilimab-csfr for carcinogenicity or genotoxicity.
Dedicated fertility studies have not been conducted with axatilimab-csfr. Administration of axatilimab-csfr to sexually mature cynomolgus monkeys in a 3-month toxicology study had no effect on menstrual cyclicity in females, sperm parameters (morphology, motility, or number) in males, and produced no histopathologic findings in female and male reproductive organs, indicating that axatilimab-csfr did not adversely affect reproductive function. Targeted deletion of CSF-1R or CSF-1 in rodent models resulted in impairment of fertility.

13.2 Animal Toxicology and/or Pharmacology

In a 6-month chronic toxicity study in sexually immature cynomolgus monkeys, axatilimab-csfr was administered once weekly at doses of 10, 30, or 100 mg/kg/week via intravenous injection. The primary findings included periorbital swelling, widespread accumulation of basophilic material, and effects on bone at doses ≥ 10 mg/kg/week. Alterations in bone included decreases in bone markers, thickening of the growth plate and metaphysis and/or degeneration of the growth plate in the femur. In a 3-month toxicity study in sexually mature monkeys, intravenous administration of axatilimab-csfr at doses of 10, 30, or 100 mg/kg/week resulted in decreases in bone biomarkers at doses ≥ 30 mg/kg/week.

14 CLINICAL STUDIES

The efficacy of NIKTIMVO was evaluated in AGAVE-201 (NCT04710576), a randomized, open-label, multicenter study in adult and pediatric patients with recurrent or refractory cGVHD who had received at least 2 lines of systemic therapy and required additional treatment. Patients with platelet count ≥ 50 × 10^9/L, absolute neutrophil count ≥ 1 × 10^9/L, ALT and AST ≤ 2.5 × ULN (≤ 5 × ULN if liver cGVHD was present), total bilirubin ≤ 1.5 × ULN, and creatinine clearance ≥ 30 mL/minute were eligible. Patients with uncontrolled infections were not eligible.
Treatment consisted of NIKTIMVO 0.3 mg/kg administered intravenously every 2 weeks until disease progression, lack of efficacy by 9 months, or unacceptable toxicity. Continued treatment with GVHD prophylaxis and standard care systemic cGVHD therapies were permitted as long as the patient had been on a stable dose for at least 2 weeks prior to study. Initiation of new systemic cGVHD therapy while on study was not permitted.
Demographics and baseline characteristics of the 79 patients treated with NIKTIMVO 0.3 mg/kg every 2 weeks in AGAVE-201 are summarized in Table 4.

Table 4: Demographics and Baseline Characteristics of Patients With cGVHD
 | NIKTIMVO 0.3 mg/kg every 2 weeks (N = 79)
Median age, years (range) | 50 (7, 76)
Age ≥ 65 years, n (%) | 21 (27)
Male, n (%) | 46 (58)
Race, n (%)
White | 67 (85)
Asian | 4 (5)
Black | 2 (3)
Other | 1 (1)
Not reported | 5 (6)
Median (range) time (months) from cGVHD diagnosis | 47 (4, 211)
≥ 4 Organs involved, n (%) | 45 (57)
Median (range) number of prior lines of therapy | 4 (2, 12)
Number of prior lines of therapy, n (%)
2 | 11 (14)
3 | 14 (18)
4 | 17 (22)
≥ 5 | 37 (47)
Prior cGVHD treatment with ibrutinib, n (%) | 27 (34)
Prior cGVHD treatment with ruxolitinib, n (%) | 57 (72)
Prior cGVHD treatment with belumosudil, n (%) | 16 (20)
Refractory to last therapy, n (%) | 37 (47)
Severe cGVHD, n (%) | 63 (80)
Median (range) Global Severity Rating | 7 (2, 10)
Median (range) modified Lee Symptom Scale Score at baseline | 24 (4, 55)
Median (range) corticosteroid dose at baseline (PE/kg) [Prednisone equivalents/kilogram/day.] | 0.21 (0.04, 2.12)

The efficacy of NIKTIMVO was based on overall response rate (ORR) through Cycle 7 Day 1, where overall response included complete response or partial response according to the 2014 NIH Consensus Development Project on Response Criteria. The ORR results from AGAVE-201 for the 0.3 mg/kg every 2 weeks dosage regimen are presented in Table 5. The median time to first response was 1.5 months (range, 0.9 to 5.1 months). The median duration of response, calculated from first response to progression, death, or new systemic therapies for cGVHD, was 1.9 months (95% CI: 1.6, 3.5). In patients who achieved response, no death or new systemic therapy initiation occurred in 60% (95% CI: 43, 74) of patients for at least 12 months since response.

Table 5: Efficacy Results From AGAVE-201
Endpoint | NIKTIMVO 0.3 mg/kg every 2 weeks (N = 79)
Overall response rate, n (%) 95% CI Complete response, n (%) Partial response, n (%) | 59 (75%) 64, 84 0 (0%) 59 (75%)
CI = confidence interval.

ORR results were supported by exploratory analyses of patient-reported symptom bother which showed at least a 7-point decrease in the modified Lee Symptom Scale score through Cycle 7 Day 1 in 56% (95% CI: 44, 67) of patients.

16 HOW SUPPLIED/STORAGE AND HANDLING

NIKTIMVO (axatilimab-csfr) injection is a slightly opalescent, pale brownish yellow solution. It is supplied in a carton containing one single-dose vial either as:

- 9 mg/0.18 mL (NDC 50881-034-12)
- 22 mg/0.44 mL (NDC 50881-023-11)
- 50 mg/mL (NDC 50881-012-10)

Store refrigerated at 2°C to 8°C (36°F to 46°F) in the original carton to protect from light. Do not freeze or shake.

17 PATIENT COUNSELING INFORMATION

Advise the patient to read the FDA-approved patient labeling (Patient Information).
Infusion-Related Reactions
Advise patients and caregivers that reactions related to the infusion may occur during NIKTIMVO treatment. Inform patients and caregivers of the signs and symptoms of infusion-related reactions and to seek medical care should signs and symptoms occur [see Warnings and Precautions (5.1)].
Embryo-Fetal Toxicity
Advise pregnant women of the potential risk to a fetus. Advise females of reproductive potential to inform their healthcare provider of a known or suspected pregnancy. Advise females of reproductive potential to use effective contraception during treatment with NIKTIMVO and for 30 days after the last dose [see Warnings and Precautions (5.2), Use in Specific Populations (8.1, 8.3)].
Lactation
Advise women not to breastfeed during treatment and for 30 days after the last dose of NIKTIMVO [see Use in Specific Populations (8.2)].
Manufactured by:
Incyte Corporation
Wilmington, DE 19803
U.S. License No.2228

Licensed from:
Syndax Pharmaceuticals, Inc.
Waltham, MA 02451

NIKTIMVO and the NIKTIMVO logo are trademarks of Incyte.
Patent Information: www.incyte.com/patents
© 2025 Incyte Corporation. All rights reserved.

PATIENT INFORMATION
NIKTIMVO™ (nik tim voe)
(axatilimab-csfr)
injection, for intravenous use

What is NIKTIMVO?

NIKTIMVO is a prescription medicine used to treat adults and children who weigh at least 88.2 pounds (40 kg) with chronic graft‑versus-host disease (cGVHD) after you have received at least 2 prior treatments (systemic therapy) and they did not work.

It is not known if NIKTIMVO is safe and effective in adults and children weighing less than 88.2 pounds (40 kg).

Before receiving NIKTIMVO, tell your healthcare provider about all of your medical conditions, including if you:

- have or have had liver problems.
- are pregnant or plan to become pregnant. NIKTIMVO may harm your unborn baby.
  Females who are able to become pregnant:
  - Your healthcare provider should do a pregnancy test before you start treatment with NIKTIMVO.
  - You should use an effective method of birth control during your treatment and for 30 days after your last dose of NIKTIMVO. Talk to your healthcare provider about birth control methods that you can use during this time.
  - Tell your healthcare provider right away if you become pregnant or think you may be pregnant during treatment with NIKTIMVO.
- are breastfeeding or plan to breastfeed. It is not known if NIKTIMVO passes into your breast milk. Do not breastfeed during treatment and for 30 days after your last dose of NIKTIMVO.

Tell your healthcare provider about all the medicines you take, including prescription and over-the-counter medicines, vitamins, and herbal supplements.

How will I receive NIKTIMVO?

- Your healthcare provider will give you NIKTIMVO through an intravenous (IV) infusion over 30 minutes.
- NIKTIMVO is given every 2 weeks.
- Your healthcare provider will decide how many treatments you will need.
- Before you receive each NIKTIMVO infusion, your healthcare provider may give you medicines called diphenhydramine and acetaminophen to help prevent infusion-related reactions.
- Your healthcare provider will do blood tests to check you for side effects.

What are the possible side effects of NIKTIMVO?

NIKTIMVO may cause serious side effects, including:

- Infusion-related reactions. Infusion-related reactions are common with NIKTIMVO and can be serious. Your healthcare provider will monitor you for infusion-related reactions during your treatment. If you have a reaction, your healthcare provider may temporarily or completely stop your treatment with NIKTIMVO. Tell your healthcare provider right away if you get fever, chills, rash, flushing, shortness of breath, trouble breathing, nausea, vomiting, or symptoms of high blood pressure such as chest pain, headaches, or blurred vision during an infusion of NIKTIMVO.

The most common side effects of NIKTIMVO include:

- infections
- increased blood level of liver enzymes
- decreased blood level of phosphate
- low red blood cell count (anemia)
- muscle, bone, or joint pain

- increased blood level of pancreatic enzymes
- low energy
- increased blood level of calcium
- increased blood level of a muscle enzyme
- increased blood level of a bone enzyme

- nausea
- headache
- diarrhea
- cough
- fever
- shortness of breath

These are not all the possible side effects of NIKTIMVO.
Call your doctor for medical advice about side effects. You may report side effects to FDA at 1 800-FDA-1088.
You may also report side effects to Incyte Corporation at 1-855-463-3463.

General information about the safe and effective use of NIKTIMVO.
Medicines are sometimes prescribed for purposes other than those listed in a Patient Information leaflet. You can ask your healthcare provider for information about NIKTIMVO that is written for health professionals.

What are the ingredients in NIKTIMVO?
Active ingredient: axatilimab-csfr
Inactive ingredients: citric acid monohydrate, glycine, polysorbate 80, sodium citrate, sucrose, and Water for Injection.

Manufactured by: Incyte Corporation, Wilmington, DE 19803
U.S. License No.2228

Licensed from: Syndax Pharmaceuticals, Inc., Waltham, MA 02451
NIKTIMVO and the NIKTIMVO logo are trademarks of Incyte.
© 2025 Incyte Corporation. All rights reserved.
For more information, call 1-855-463-3463 or go to www.incyte.com/patents.

This Patient Information has been approved by the U.S. Food and Drug Administration. Issued: 1/2025

NIKTIMVO 50 MG/ML CARTON

NDC 50881-012-10
Rx Only

NIKTIMVO™
(axatilimab-csfr)
Injection
50 mg/mL

For intravenous infusion after dilution.
Contains one 1 mL single-dose vial.
Discard unused portion.

NIKTIMVO 9 MG/0.18ML CARTON

NDC 50881-034-12
Rx Only

NIKTIMVO™
(axatilimab-csfr)
Injection
9 mg/0.18mL

For intravenous infusion after dilution.
Contains one 0.18 mL single-dose vial.
Discard unused portion.

NIKTIMVO 22 MG/0.44ML CARTON

NDC 50881-023-11
Rx Only

NIKTIMVO™
(axatilimab-csfr)
Injection
22 mg/0.44mL

For intravenous infusion after dilution.
Contains one 0.44 mL single-dose vial.
Discard unused portion.